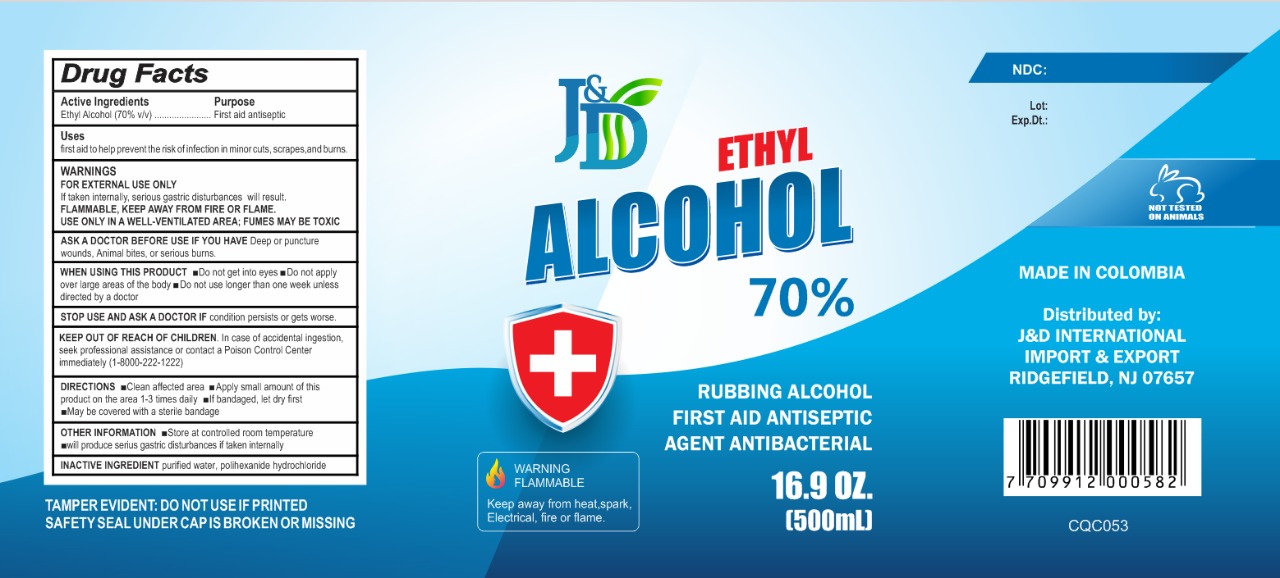 DRUG LABEL: ETHYL ALCOHOL 70%
NDC: 82628-1002 | Form: LOTION
Manufacturer: COSMOQUIMICA LAB SAS
Category: otc | Type: HUMAN OTC DRUG LABEL
Date: 20220420

ACTIVE INGREDIENTS: ALCOHOL 500 mL/500 mL

ETANOL

TOPIC

DO NOT GET INTO EYES, DO NOT APPLY OVER LARGE AREAS OF THE BODY; DO NOT USE LONGER THAN ONE WEEK UNIESS DIRECTED BY DOCTOR

IN CASE OF ACCIDENTAL INGESTION, SEEK PROFESSIONAL ASSISTANCE OR CONTACT A POISON CONTROL CENTER INMMEDIATELY (1-8000-222-1222)

FIRST AID ANTISEPTIC

DEEP OR PUNCTURE, WOUNDS, ANIMAL BRITES, OR SERIUOS BURNS. STOP USE AND ASK A DOCTOR IF CONDITION PERSISTS OR GETS WORSE